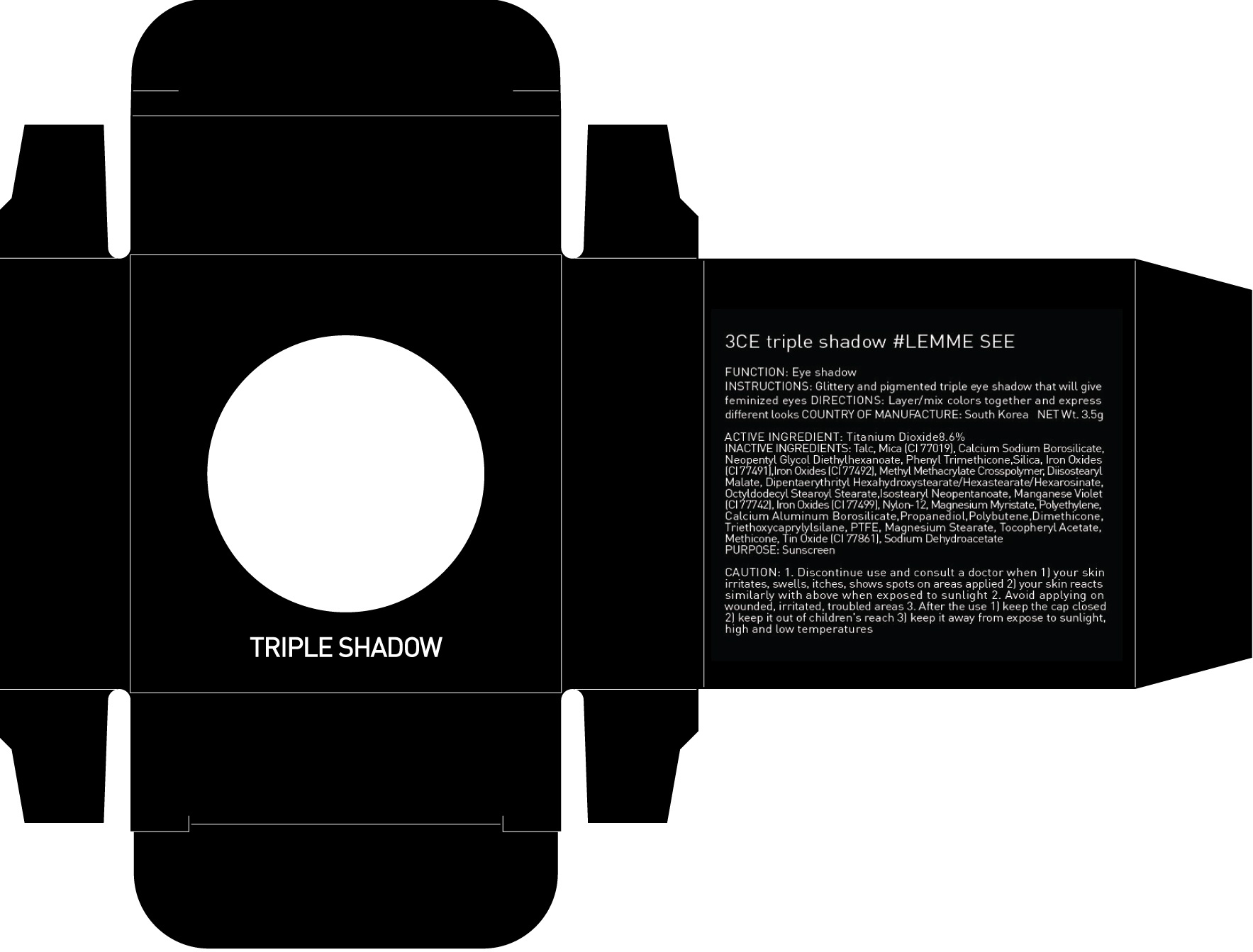 DRUG LABEL: 3CE TRIPLE SHADOW LEMME SEE
NDC: 60764-023 | Form: POWDER
Manufacturer: Nanda Co., Ltd
Category: otc | Type: HUMAN OTC DRUG LABEL
Date: 20160922

ACTIVE INGREDIENTS: Titanium Dioxide 0.30 g/3.5 g
INACTIVE INGREDIENTS: Talc; Mica

ACTIVE INGREDIENT

Active Ingredient: Titanium Dioxide 8.6%

INACTIVE INGREDIENT

Inactive Ingredients: Talc, Mica (CI 77019), Calcium Sodium Borosilicate, Neopentyl Glycol Diethylhexanoate, Phenyl Trimethicone,Silica, Iron Oxides (CI 77491),Iron Oxides (CI 77492), Methyl Methacrylate Crosspolymer, Diisostearyl Malate, Dipentaerythrityl Hexahydroxystearate/Hexastearate/Hexarosinate, Octyldodecyl Stearoyl Stearate,Isostearyl Neopentanoate, Manganese Violet (CI 77742), Iron Oxides (CI 77499), Nylon-12, Magnesium Myristate, Polyethylene, Calcium Aluminum Borosilicate,Propanediol,Polybutene,Dimethicone, Triethoxycaprylylsilane, PTFE, Magnesium Stearate, Tocopheryl Acetate, Methicone, Tin Oxide (CI 77861), Sodium Dehydroacetate

PURPOSE

Purpose: Sunscreen

CAUTION

CAUTION: 1. Discontinue use and consult a doctor when - your skin irritates, swells, itches, shows spots on areas applied - your skin reacts similarly with above when exposed to sunlight 2. Avoid applying on wounded, irritated, troubled areas 3. After the use - keep the cap closed - keep it out of children's reach - keep it away from expose to sunlight, high and low temperatures

DESCRIPTION

INSTRUCTIONS: Glittery and pigmented triple eye shadow that will give feminized eyes.

Directions: Layer/mix colors together and express different looks